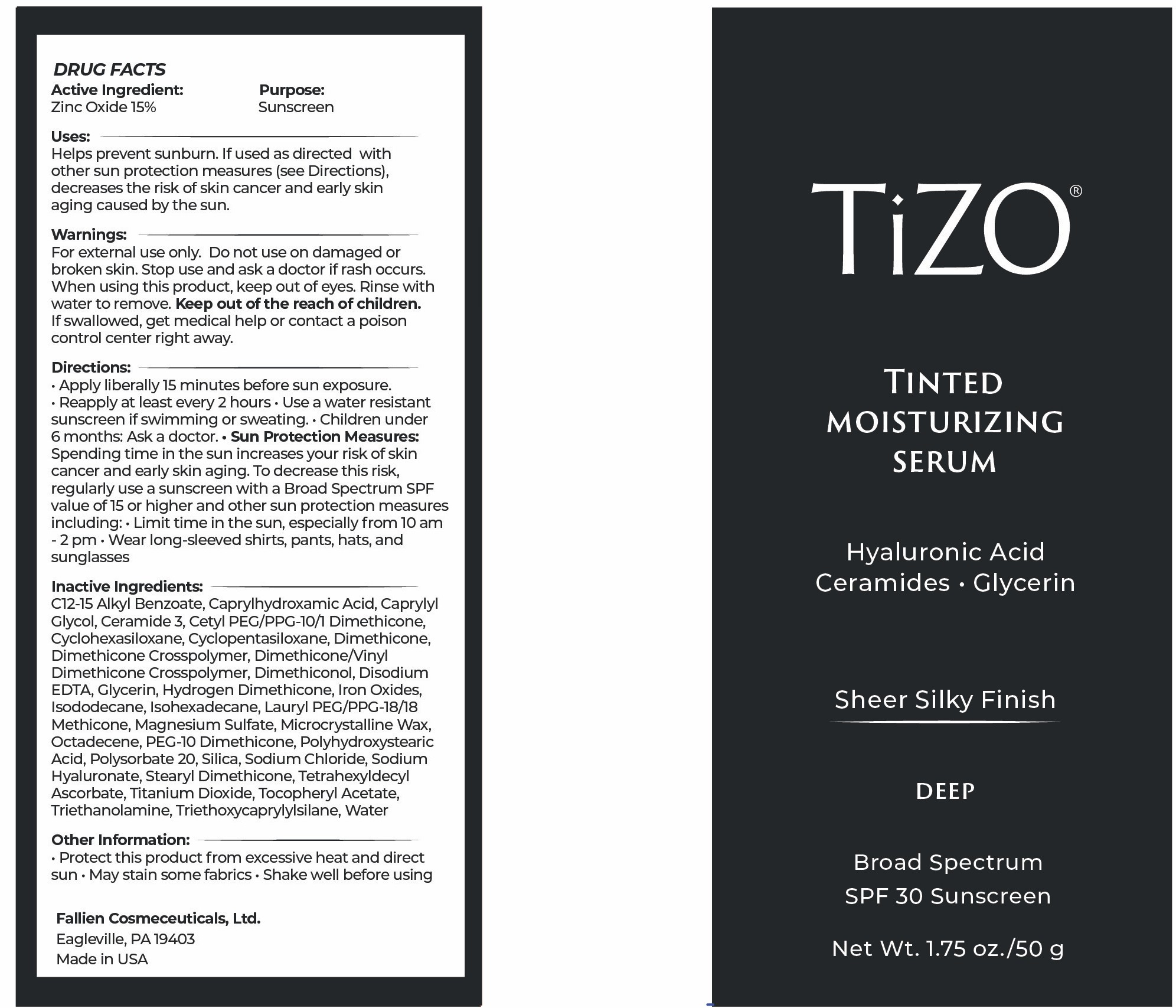 DRUG LABEL: TiZO Tinted Moisturizing Serum - Deep
NDC: 58892-135 | Form: CREAM
Manufacturer: Fallien Cosmeceuticals, Ltd.
Category: otc | Type: HUMAN OTC DRUG LABEL
Date: 20251216

ACTIVE INGREDIENTS: ZINC OXIDE 150 mg/1 g
INACTIVE INGREDIENTS: CERAMIDE 3; DIMETHICONE; DIMETHICONOL (2000 CST); HYDROGEN DIMETHICONE (20 CST); LAURYL PEG/PPG-18/18 METHICONE; OCTADECENE; SILICON DIOXIDE; SODIUM HYALURONATE; POLYSORBATE 20; DIMETHICONE/VINYL DIMETHICONE CROSSPOLYMER (SOFT PARTICLE); EDETATE DISODIUM ANHYDROUS; CYCLOPENTASILOXANE; TRIETHOXYCAPRYLYLSILANE; WATER; TRIETHANOLAMINE; C12-15 ALKYL BENZOATE; CAPRYLYL GLYCOL; CYCLOHEXASILOXANE; DIMETHICONE CROSSPOLYMER; CI 77491; MICROCRYSTALLINE WAX; TITANIUM DIOXIDE; CAPRYLHYDROXAMIC ACID; CETYL PEG/PPG-10/1 DIMETHICONE (HLB 4); MAGNESIUM SULFATE; GLYCERIN; ISODODECANE; PEG-10 DIMETHICONE (600 CST); SODIUM CHLORIDE; STEARYL DIMETHICONE (400 MPA.S AT 50C); TETRAHEXYLDECYL ASCORBATE; ALPHA-TOCOPHEROL ACETATE; ISOHEXADECANE; POLYHYDROXYSTEARIC ACID (2300 MW); CI 77492; CI 77499

Active Ingredients:

Zinc Oxide 15%

Purpose:

Sunscreen

Uses:

Helps prevents sunburn. If used as directed with other sun protection measures (see Directions), decreases the risk of skin cancer and early skin aging caused by the sun.

Warnings:

For external use only. Do not use on damaged or broken skin. Stop use and ask a doctor if rash occurs. When using this product, keep out of eyes. Rinse with water to remove. Keep out of the reach of children. If swallowed, get medical help or contact a poison control center right away.

Directions:

Apply liberally 15 minutes before sun exposure. Use a water resistant product if swimming or sweating. Reapply At least every 2 hours. Children under 6 months: Ask a doctor. Sun Protection Measures: Spending time in the sun increases your risk of skin cancer and early skin aging. To decrease this risk, regularly use a sunscreen with a Broad Spectrum SPF value of 15 or higher and other sun protection measures including: Limit time in the sun, especially from 10 a.m. - 2 p.m. Wear long-sleeved shirts, pants, hats, and sunglasses

Inactive Ingredients:

C 12-15 Alkyl Benzoate, Caprylhydroxamic Acid, Caprylyl Glycol, Ceramide 3, CetylPEG/PPG-10/1 Dimethicone, Cyclohexasiloxane, Cyclopentasiloxane, Dimethicone,Dimethicone Crosspolymer, Dimethicone/Vinyl Dimethicone Crosspolymer, Dimethiconol, Disodium EDTA, Glycerin, Hydrogen Dimethicone, Iron Oxides, Isododecane, Isohexadecane, Lauryl PEG/PPG-18/18 Methicone, Magnesium Sulfate, Microcrystalline Wax, Octadecene, PEG-10 Dimethicone, Polyhydroxystearic Acid, Polysorbate 20, Silica, Sodium Chloride, Sodium Hyaluronate, Stearyl Dimethicone, Tetrahexyldecyl Ascorbate, Titanium Dioxide,
Tocopheryl Acetate, Triethanolamine, Triethoxycaprylylsilane, Water

Other Information:

Protect this product from excessive heat and direct sun. May stain some fabrics. Shake well before using.

Warning:

Keep out of the freach of children.